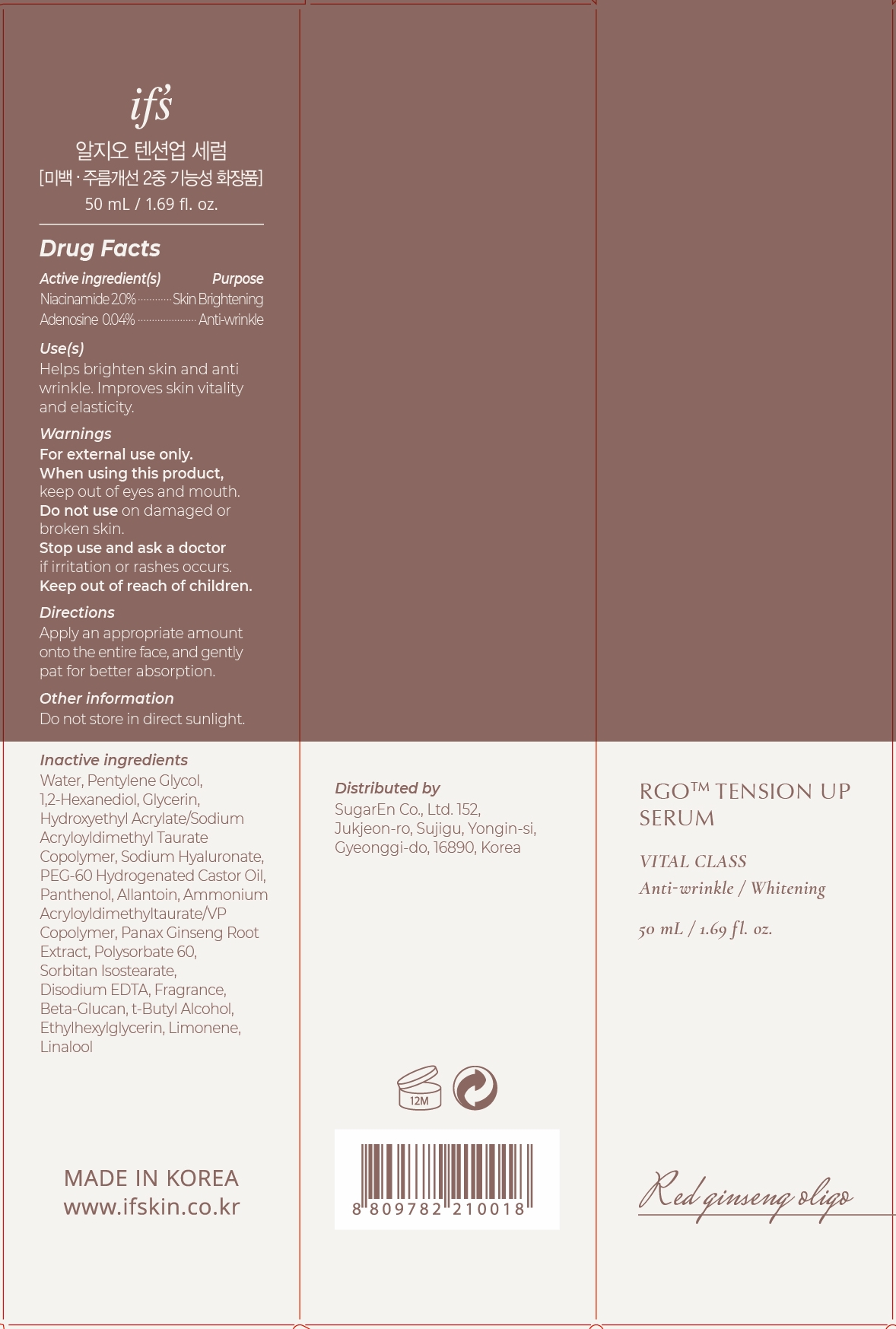 DRUG LABEL: RGO TENSION UP SERUM
NDC: 81897-502 | Form: LIQUID
Manufacturer: SugarEn Co., Ltd.
Category: otc | Type: HUMAN OTC DRUG LABEL
Date: 20210529

ACTIVE INGREDIENTS: NIACINAMIDE 2 g/100 mL; ADENOSINE 0.04 g/100 mL
INACTIVE INGREDIENTS: PENTYLENE GLYCOL; HYDROXYETHYL ACRYLATE/SODIUM ACRYLOYLDIMETHYL TAURATE COPOLYMER (45000 MPA.S AT 1%); TERT-BUTYL ALCOHOL; LINALOOL, (+/-)-; GLYCERIN; EDETATE DISODIUM ANHYDROUS; WATER; 1,2-HEXANEDIOL; SORBITAN ISOSTEARATE; HYALURONATE SODIUM; POLYOXYL 60 HYDROGENATED CASTOR OIL; PANTHENOL; ALLANTOIN; AMMONIUM ACRYLOYLDIMETHYLTAURATE/VP COPOLYMER; ASIAN GINSENG; POLYSORBATE 60; LIMONENE, (+)-; ETHYLHEXYLGLYCERIN

81897-502 RGO TENSION UP SERUM

Active ingredient(s)

Niacinamide 2.0%

Adenosine 0.04%

Purpose

Skin Brightening, Anti-wrinkle

Use(s)

Helps brighten skin and anti wrinkle.

Improves skin vitality and elasticity.

Warnings

For external only.

When using this product,

keep out of eyes and mouth.

Do not use

on damaged or broken skin.

Stop use and ask a doctor

if irritation or rashes occurs.

Keep out of reach of children.

Other information

Do not store in direct sunlight.

Directions

Apply an appropriate amount onto the entire face, and gently pat for better absorption.

Inactive indredients

Water, Pentylene Glycol, 1,2-Hexanediol, Glycerin, Hydroxyethyl Acrylate/Sodium Acryloyldimethyl Taurate Copolymer, Sodium Hyaluronate, PEG-60 Hydrogenated Castor Oil, Panthenol, Allantoin, Ammonium Acryloyldimethyltaurate/VP Copolymer, Panax Ginseng Root Extract, Polysorbate 60, Sorbitan Isostearate, Disodium EDTA, Fragrance, Beta-Glucan, t-Butyl Alcohol, Ethylhexylglycerin, Limonene, Linalool